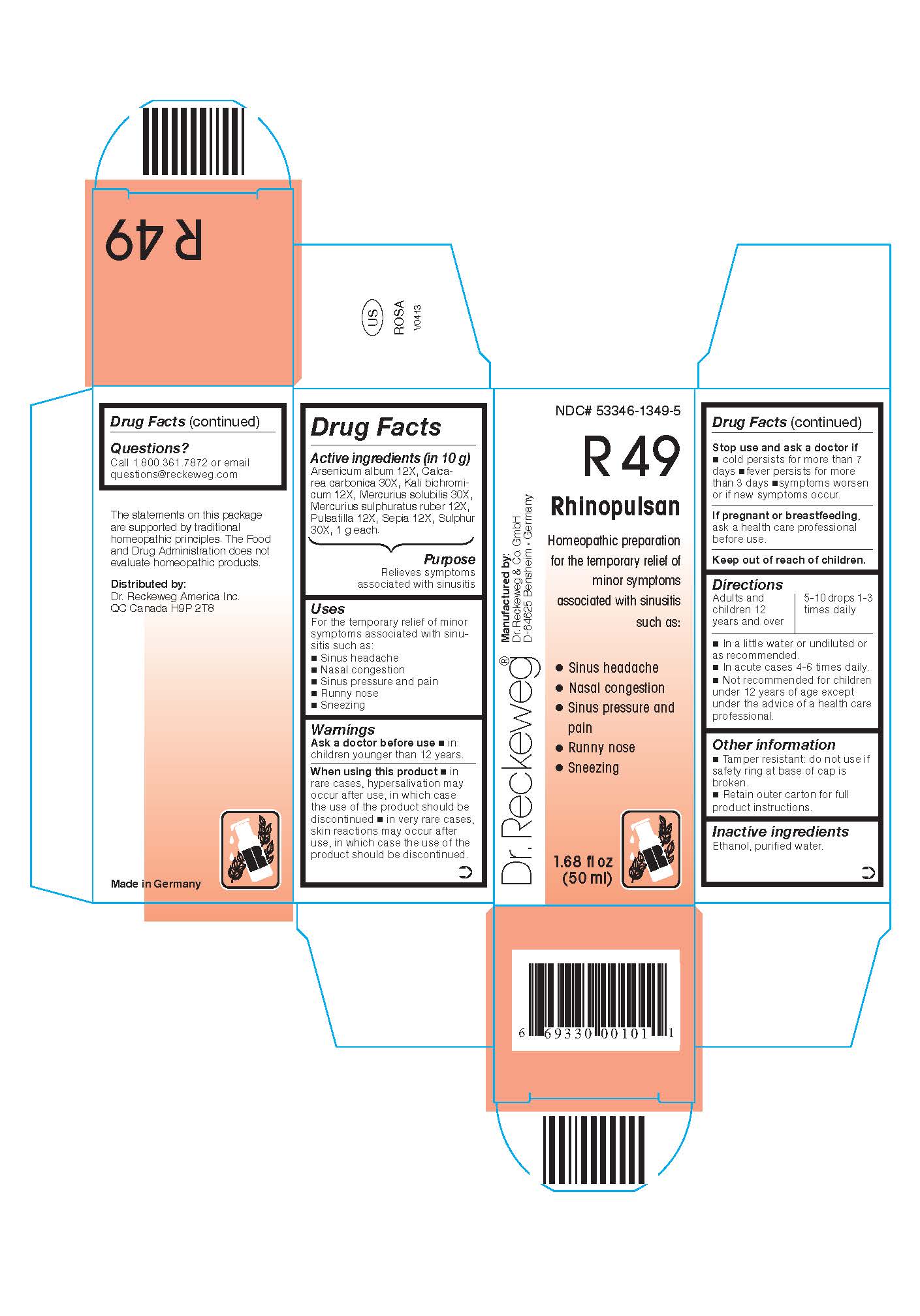 DRUG LABEL: DR. RECKEWEG R49 Rhinopulsan
NDC: 53346-1349 | Form: LIQUID
Manufacturer: PHARMAZEUTISCHE FABRIK DR. RECKEWEG & CO
Category: homeopathic | Type: HUMAN OTC DRUG LABEL
Date: 20130405

ACTIVE INGREDIENTS: ARSENIC TRIOXIDE 12 [hp_X]/50 mL; OYSTER SHELL CALCIUM CARBONATE, CRUDE 30 [hp_X]/50 mL; POTASSIUM DICHROMATE 12 [hp_X]/50 mL; MERCURIUS SOLUBILIS 30 [hp_X]/50 mL; MERCURIC SULFIDE 12 [hp_X]/50 mL; PULSATILLA PRATENSIS 12 [hp_X]/50 mL; SEPIA OFFICINALIS JUICE 12 [hp_X]/50 mL; SULFUR 30 [hp_X]/50 mL
INACTIVE INGREDIENTS: ALCOHOL; WATER

DR. RECKEWEG R49 Rhinopulsan

Active ingredients:

Arsenicum album 12X, Calcarea carbonica 30X, Kali bichromicum 12X, Mercurius solubilis 30X, Mercurius sulphuratus ruber 12X, Pulsatilla 12X, Sepia 12X, Sulphur 30X, 1 g each in 10 g.

Purpose

Relieves symptoms associated with sinusitis

Uses
For the temporary relief of minor symptoms associated with sinusitis such as:

- Sinus headache
- Nasal congestion
- Sinus pressure and pain
- Runny nose
- Sneezing

Warnings

Ask a doctor before use

- in children younger than 12 years.

When using this product

- in rare cases, hypersalivation may occur after use, in which case the use of the product should be discontinued
- in very rare cases, skin reactions may occur after use, in which case the product should be discontinued.

Stop use and ask a doctor if

- cold persists for more than 7 days
- fever persists for more than 3 days
- symptoms worsen or if new symptoms occur.

PREGNANCY OR BREAST FEEDING

If pregnant or breastfeeding, ask a health care professional before use.

Keep out of reach of children.

Directions
Adults and children ≥ 12 years 5-10 drops 1-3 times daily, acute cases 4-6 times daily in a little water or undiluted or as recommended.

Not recommended for children under 12 years of age except under the advice of a health care professional.

Other information
Tamper resistant: do not use if safety ring at base of cap is broken.

Retain outer carton for full product instructions.

Inactive ingredients

Ethanol, purified water.

Questions?

Call 1-800-361-7872 or email questions@reckeweg.co

PACKAGE LABEL

NDC# 53346-1349-5

Dr. Reckeweg R49 Rhinopulsan

Homeopathic preparation for the temporary relief of minor symptoms associated with sinusitis such as:

- Sinus headache
- Nasal congestion
- Sinus pressure and pain
- Runny nose
- Sneezing

Manufactured by:

Dr. Reckeweg Co. GmbH

D-64625 Bensheim

Germany

1.68 fl oz
(50 ml)